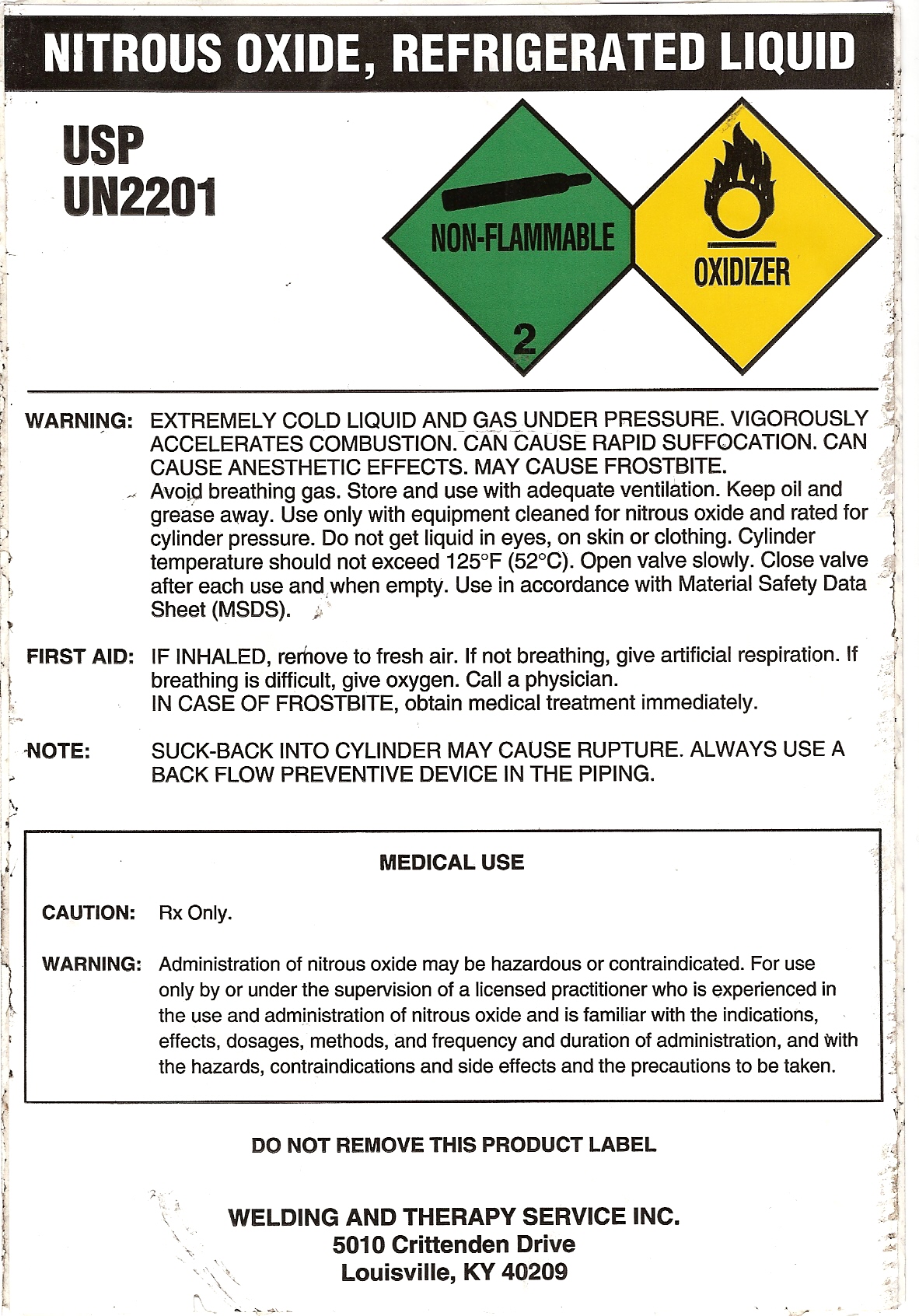 DRUG LABEL: Nitrous Oxide
NDC: 33344-004 | Form: LIQUID
Manufacturer: Welding & Therapy Service Inc.
Category: prescription | Type: HUMAN PRESCRIPTION DRUG LABEL
Date: 20110722

ACTIVE INGREDIENTS: Nitrous Oxide 99 L/100 L

NITROUS OXIDE, REFRIGERATED LIQUID LABEL

PACKAGE LABEL

NITROUS OXIDE, REFRIGERATED LIQUID
USP
UN2201
NON-FLAMMABLE 2 OXIDIZER
WARNING: EXTREMELY COLD LIQUID AND GAS UNDER PRESSURE. VIGOROUSLY
ACCELERATES COMBUSTION. CAN CAUSE RAPID SUFFOCATION. CAN
CAUSE ANESTHETIC EFFECTS. MAY CAUSE FROSTBITE.
Avoid breathing gas. Store and use with adequate ventilation. Keep oil and
grease away. Use only with equipment cleaned for nitrous oxide and rated for
cylinder pressure. Do not get liquid in eyes, on skin or clothing. Cylinder
temperature should not exceed 125oF (52oC). Open valve slowly. Close valve
after each use and when empty. Use in accordance with Material Safty Data
Sheet (MSDS).
FIRST AID: IF INHALED, remove to fresh air. If not breathing, give artificial respiration. If
breathing is difficult, give oxygen. Call a physician.
IN CASE OF FROSTBITE, obtain medical treatment immediately.
NOTE: SUCK-BACK INTO CYLINDER MAY CAUSE RUPTURE. ALWAYS USE A
BACK FLOW PREVENTIVE DEVICE IN THE PIPING.
MEDICAL USE
CAUTION: Rx Only
WARNING: Administration of nitrous oxide may be hazardous or contraindicated. For use
only by or under the supervision of a licensed practitioner who is experienced in
the use and administration of nitrous oxide and is familiar with the indications,
effects, dosages, methods, and frequency and duration of administration, and with
the hazards, contraindications and side effects and the precautions to be taken.
DO NOT REMOVE THIS PRODUCT LABEL
WELDING AND THERAPY SERVICE INC.
5010 Crittenden Drive
Louisville, KY 40209